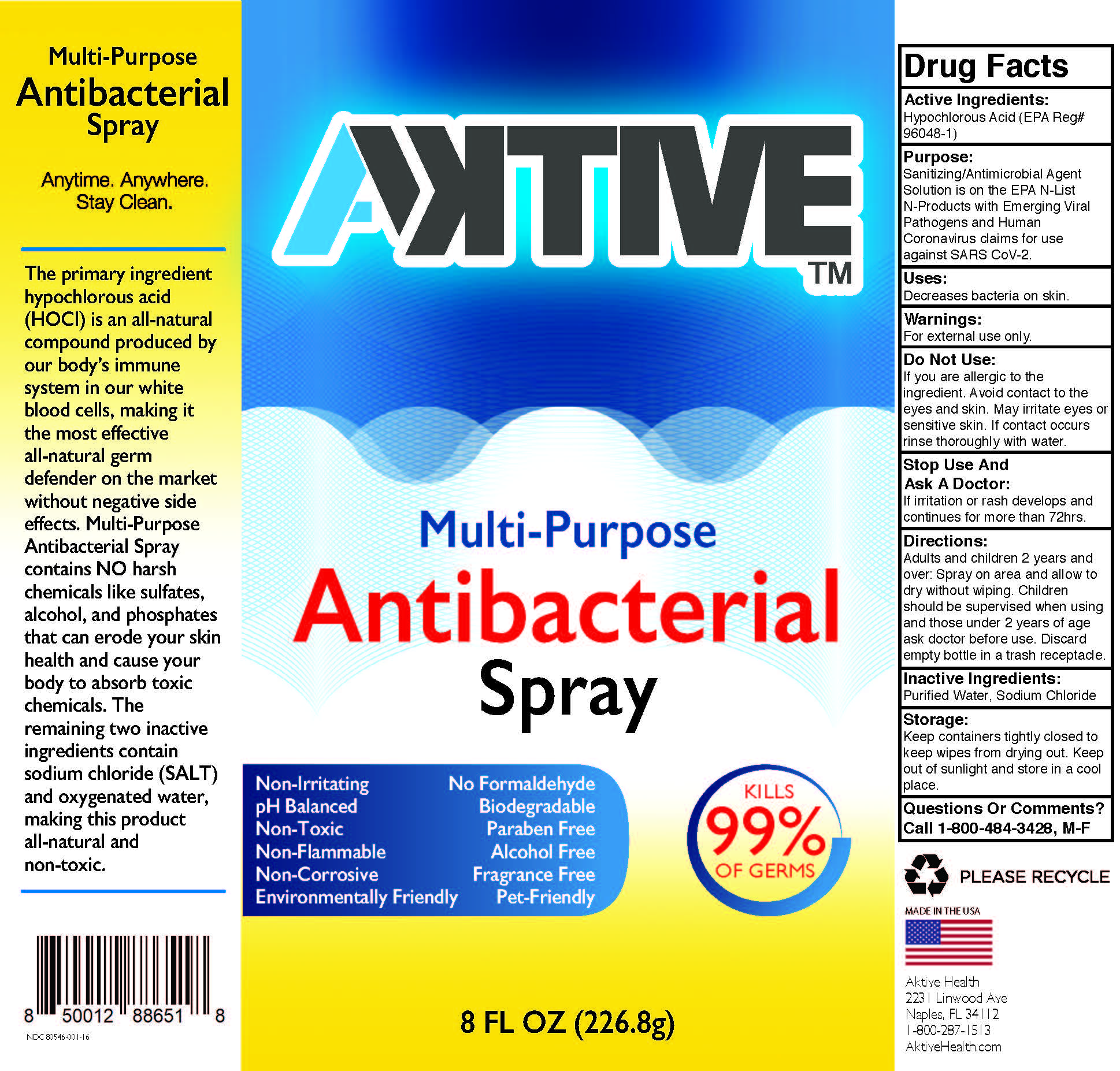 DRUG LABEL: Aktive Multi Purpose Antibacterial
NDC: 81156-002 | Form: LIQUID
Manufacturer: Hall Global LLC
Category: otc | Type: HUMAN OTC DRUG LABEL
Date: 20201124

ACTIVE INGREDIENTS: HYPOCHLOROUS ACID 0.25 mg/100 mg
INACTIVE INGREDIENTS: SODIUM CHLORIDE 3.05 mg/100 mg; WATER

Spray

This is a Antibacterilal Spray manufactured according to the Temporary Policy for Preparation of Certain Alcohol-Based Hand Sanitizer Products During the Public Health Emergency (CoViD-19); Guidance for Industry.

The Antibacterilal Spray is manufactured using only the following United States Pharmacopoeia (USP) grade ingredients in the preparation of the product (percentage in final product formulation) consistent with World Health Organization (WHO) recommendations:

1. Hypochlorous Acid (EPA Reg# 96048-1) (USP or Food Chemical Codex (FCC) grade) (80%, volume/volume (v/v)) in an aqueous solution denatured according to Alcohol and Tobacco Tax and Trade Bureau regulations in 27 CFR part 20.
2. Sterile distilled water or boiled cold water.
3. Sodium Chloride

The firm does not add other active or inactive ingredients. Different or additional ingredients may impact the quality and potency of the product.

Active Ingredient(s)

Hypochlorous Acid (EPA Reg# 96048-1)

Purpose

Sanitizing/Antimicrobial Agent Solution is on the EPA N-List N-Product with Emerging Viral Pathogens and Human Coronavirus claims for use against SARS CoV-2

Use

Decreases bacteria on skin.

Warnings

For external use only.

Do not use

If you are allergic to the ingredient. Avoid contact to the eyes and skin. May irritate eyes or sensitive skin. If contact occurs rinse thoroughly with water.

When using this product keep out of eyes, ears, and mouth. In case of contact with eyes, rinse eyes thoroughly with water.
Stop use and ask a doctor if irritation or rash occurs. These may be signs of a serious condition.
Keep out of reach of children. If swallowed, get medical help or contact a Poison Control Center right away.

Stop use and ask a doctor if irritation or rash develops and continues for more than 72 hrs

Keep out of reach of children. If swallowed, get medical help or contact a Poison Control Center right away.

Directions

Adults and children 2 years and over: Spray on area and allow to dry without wiping. Children should be supervised when using and those under 2 years of age ask doctor before use. Discard empty bottle in trash receptacle.

Other information

- Store between 15-30C (59-86F)
- Avoid freezing and excessive heat above 40C (104F)

Inactive ingredients

purified water, Sodium Clhoride

Package Label - Principal Display Panel

000 mL NDC: 00000-000-00